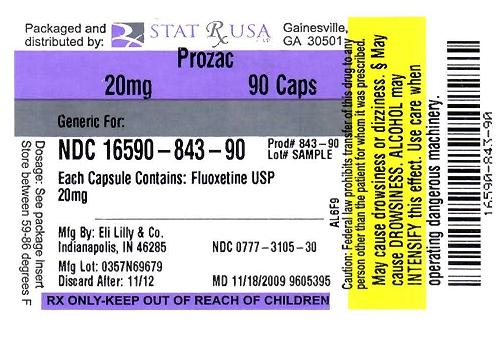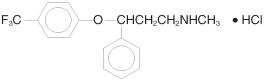 DRUG LABEL: Prozac
NDC: 16590-843 | Form: CAPSULE
Manufacturer: Stat Rx USA
Category: prescription | Type: HUMAN PRESCRIPTION DRUG LABEL
Date: 20091027

ACTIVE INGREDIENTS: Fluoxetine hydrochloride 20 mg/1 1

Prozac (Fluoxetine hydrochloride) capsule

CLINICAL PHARMACOLOGYPharmacodynamics

The antidepressant, antiobsessive compulsive, and antibulimic actions of fluoxetine are presumed to be linked to its inhibition of CNS neuronal uptake of serotonin. Studies at clinically relevant doses in man have demonstrated that fluoxetine blocks the uptake of serotonin into human platelets. Studies in animals also suggest that fluoxetine is a much more potent uptake inhibitor of serotonin than of norepinephrine.

Antagonism of muscarinic, histaminergic, and α1–adrenergic receptors has been hypothesized to be associated with various anticholinergic, sedative, and cardiovascular effects of classical tricyclic antidepressant (TCA) drugs. Fluoxetine binds to these and other membrane receptors from brain tissue much less potently in vitro than do the tricyclic drugs.

Absorption, Distribution, Metabolism, and Excretion

Systemic bioavailability — In man, following a single oral 40–mg dose, peak plasma concentrations of fluoxetine from 15 to 55 ng/mL are observed after 6 to 8 hours.

The Pulvule, oral solution, and Prozac Weekly capsule dosage forms of fluoxetine are bioequivalent. Food does not appear to affect the systemic bioavailability of fluoxetine, although it may delay its absorption by 1 to 2 hours, which is probably not clinically significant. Thus, fluoxetine may be administered with or without food. Prozac Weekly capsules, a delayed–release formulation, contain enteric–coated pellets that resist dissolution until reaching a segment of the gastrointestinal tract where the pH exceeds 5.5. The enteric coating delays the onset of absorption of fluoxetine 1 to 2 hours relative to the immediate–release formulations.

Protein binding — Over the concentration range from 200 to 1000 ng/mL, approximately 94.5% of fluoxetine is bound in vitro to human serum proteins, including albumin and α1–glycoprotein. The interaction between fluoxetine and other highly protein–bound drugs has not been fully evaluated, but may be important (see PRECAUTIONS).

Enantiomers — Fluoxetine is a racemic mixture (50/50) of R–fluoxetine and S–fluoxetine enantiomers. In animal models, both enantiomers are specific and potent serotonin uptake inhibitors with essentially equivalent pharmacologic activity. The S–fluoxetine enantiomer is eliminated more slowly and is the predominant enantiomer present in plasma at steady state.

Metabolism — Fluoxetine is extensively metabolized in the liver to norfluoxetine and a number of other unidentified metabolites. The only identified active metabolite, norfluoxetine, is formed by demethylation of fluoxetine. In animal models, S–norfluoxetine is a potent and selective inhibitor of serotonin uptake and has activity essentially equivalent to R– or S–fluoxetine. R–norfluoxetine is significantly less potent than the parent drug in the inhibition of serotonin uptake. The primary route of elimination appears to be hepatic metabolism to inactive metabolites excreted by the kidney.

Clinical issues related to metabolism/elimination — The complexity of the metabolism of fluoxetine has several consequences that may potentially affect fluoxetine’s clinical use.

Variability in metabolism — A subset (about 7%) of the population has reduced activity of the drug metabolizing enzyme cytochrome P450 2D6 (CYP2D6). Such individuals are referred to as “poor metabolizers” of drugs such as debrisoquin, dextromethorphan, and the TCAs. In a study involving labeled and unlabeled enantiomers administered as a racemate, these individuals metabolized S–fluoxetine at a slower rate and thus achieved higher concentrations of S–fluoxetine. Consequently, concentrations of S–norfluoxetine at steady state were lower. The metabolism of R–fluoxetine in these poor metabolizers appears normal. When compared with normal metabolizers, the total sum at steady state of the plasma concentrations of the 4 active enantiomers was not significantly greater among poor metabolizers. Thus, the net pharmacodynamic activities were essentially the same. Alternative, nonsaturable pathways (non–2D6) also contribute to the metabolism of fluoxetine. This explains how fluoxetine achieves a steady–state concentration rather than increasing without limit.

Because fluoxetine’s metabolism, like that of a number of other compounds including TCAs and other selective serotonin reuptake inhibitors (SSRIs), involves the CYP2D6 system, concomitant therapy with drugs also metabolized by this enzyme system (such as the TCAs) may lead to drug interactions (see Drug Interactions under PRECAUTIONS).

Accumulation and slow elimination — The relatively slow elimination of fluoxetine (elimination half–life of 1 to 3 days after acute administration and 4 to 6 days after chronic administration) and its active metabolite, norfluoxetine (elimination half–life of 4 to 16 days after acute and chronic administration), leads to significant accumulation of these active species in chronic use and delayed attainment of steady state, even when a fixed dose is used. After 30 days of dosing at 40 mg/day, plasma concentrations of fluoxetine in the range of 91 to 302 ng/mL and norfluoxetine in the range of 72 to 258 ng/mL have been observed. Plasma concentrations of fluoxetine were higher than those predicted by single–dose studies, because fluoxetine’s metabolism is not proportional to dose. Norfluoxetine, however, appears to have linear pharmacokinetics. Its mean terminal half–life after a single dose was 8.6 days and after multiple dosing was 9.3 days. Steady–state levels after prolonged dosing are similar to levels seen at 4 to 5 weeks.

The long elimination half–lives of fluoxetine and norfluoxetine assure that, even when dosing is stopped, active drug substance will persist in the body for weeks (primarily depending on individual patient characteristics, previous dosing regimen, and length of previous therapy at discontinuation). This is of potential consequence when drug discontinuation is required or when drugs are prescribed that might interact with fluoxetine and norfluoxetine following the discontinuation of Prozac.

Weekly dosing — Administration of Prozac Weekly once weekly results in increased fluctuation between peak and trough concentrations of fluoxetine and norfluoxetine compared with once–daily dosing [for fluoxetine: 24% (daily) to 164% (weekly) and for norfluoxetine: 17% (daily) to 43% (weekly)]. Plasma concentrations may not necessarily be predictive of clinical response. Peak concentrations from once–weekly doses of Prozac Weekly capsules of fluoxetine are in the range of the average concentration for 20–mg once–daily dosing. Average trough concentrations are 76% lower for fluoxetine and 47% lower for norfluoxetine than the concentrations maintained by 20–mg once–daily dosing. Average steady–state concentrations of either once–daily or once–weekly dosing are in relative proportion to the total dose administered. Average steady–state fluoxetine concentrations are approximately 50% lower following the once–weekly regimen compared with the once–daily regimen.

Cmax for fluoxetine following the 90–mg dose was approximately 1.7–fold higher than the Cmax value for the established 20–mg once–daily regimen following transition the next day to the once–weekly regimen. In contrast, when the first 90–mg once–weekly dose and the last 20–mg once–daily dose were separated by 1 week, Cmax values were similar. Also, there was a transient increase in the average steady–state concentrations of fluoxetine observed following transition the next day to the once–weekly regimen. From a pharmacokinetic perspective, it may be better to separate the first 90–mg weekly dose and the last 20–mg once–daily dose by 1 week (see DOSAGE AND ADMINISTRATION).

Liver disease — As might be predicted from its primary site of metabolism, liver impairment can affect the elimination of fluoxetine. The elimination half–life of fluoxetine was prolonged in a study of cirrhotic patients, with a mean of 7.6 days compared with the range of 2 to 3 days seen in subjects without liver disease; norfluoxetine elimination was also delayed, with a mean duration of 12 days for cirrhotic patients compared with the range of 7 to 9 days in normal subjects. This suggests that the use of fluoxetine in patients with liver disease must be approached with caution. If fluoxetine is administered to patients with liver disease, a lower or less frequent dose should be used (see PRECAUTIONS and DOSAGE AND ADMINISTRATION).

Renal disease — In depressed patients on dialysis (N=12), fluoxetine administered as 20 mg once daily for 2 months produced steady–state fluoxetine and norfluoxetine plasma concentrations comparable with those seen in patients with normal renal function. While the possibility exists that renally excreted metabolites of fluoxetine may accumulate to higher levels in patients with severe renal dysfunction, use of a lower or less frequent dose is not routinely necessary in renally impaired patients (see Use in Patients with Concomitant Illness under PRECAUTIONS and DOSAGE AND ADMINISTRATION).

Age

Geriatric pharmacokinetics — The disposition of single doses of fluoxetine in healthy elderly subjects (>65 years of age) did not differ significantly from that in younger normal subjects. However, given the long half–life and nonlinear disposition of the drug, a single–dose study is not adequate to rule out the possibility of altered pharmacokinetics in the elderly, particularly if they have systemic illness or are receiving multiple drugs for concomitant diseases. The effects of age upon the metabolism of fluoxetine have been investigated in 260 elderly but otherwise healthy depressed patients (≥60 years of age) who received 20 mg fluoxetine for 6 weeks. Combined fluoxetine plus norfluoxetine plasma concentrations were 209.3 ± 85.7 ng/mL at the end of 6 weeks. No unusual age–associated pattern of adverse events was observed in those elderly patients.

INDICATIONS AND USAGEMajor Depressive Disorder

Prozac is indicated for the treatment of major depressive disorder.

Adult — The efficacy of Prozac was established in 5– and 6–week trials with depressed adult and geriatric outpatients (≥18 years of age) whose diagnoses corresponded most closely to the DSM–III (currently DSM–IV) category of major depressive disorder (see CLINICAL TRIALS).

A major depressive episode (DSM–IV) implies a prominent and relatively persistent (nearly every day for at least 2 weeks) depressed or dysphoric mood that usually interferes with daily functioning, and includes at least 5 of the following 9 symptoms: depressed mood, loss of interest in usual activities, significant change in weight and/or appetite, insomnia or hypersomnia, psychomotor agitation or retardation, increased fatigue, feelings of guilt or worthlessness, slowed thinking or impaired concentration, a suicide attempt or suicidal ideation.

The effects of Prozac in hospitalized depressed patients have not been adequately studied.

The efficacy of Prozac 20 mg once daily in maintaining a response in major depressive disorder for up to 38 weeks following 12 weeks of open–label acute treatment (50 weeks total) was demonstrated in a placebo–controlled trial.

The efficacy of Prozac Weekly once weekly in maintaining a response in major depressive disorder has been demonstrated in a placebo–controlled trial for up to 25 weeks following open–label acute treatment of 13 weeks with Prozac 20 mg daily for a total treatment of 38 weeks. However, it is unknown whether or not Prozac Weekly given on a once–weekly basis provides the same level of protection from relapse as that provided by Prozac 20 mg daily (see CLINICAL TRIALS).

Pediatric (children and adolescents) — The efficacy of Prozac in children and adolescents was established in two 8– to 9–week placebo–controlled clinical trials in depressed outpatients whose diagnoses corresponded most closely to the DSM–III–R or DSM–IV category of major depressive disorder (see CLINICAL TRIALS).

The usefulness of the drug in adult and pediatric patients receiving fluoxetine for extended periods should be reevaluated periodically.

Obsessive Compulsive Disorder

Adult — Prozac is indicated for the treatment of obsessions and compulsions in patients with obsessive compulsive disorder (OCD), as defined in the DSM–III–R; i.e., the obsessions or compulsions cause marked distress, are time–consuming, or significantly interfere with social or occupational functioning.

The efficacy of Prozac was established in 13–week trials with obsessive compulsive outpatients whose diagnoses corresponded most closely to the DSM–III–R category of OCD (see CLINICAL TRIALS).

OCD is characterized by recurrent and persistent ideas, thoughts, impulses, or images (obsessions) that are ego–dystonic and/or repetitive, purposeful, and intentional behaviors (compulsions) that are recognized by the person as excessive or unreasonable.

The effectiveness of Prozac in long–term use, i.e., for more than 13 weeks, has not been systematically evaluated in placebo–controlled trials. Therefore, the physician who elects to use Prozac for extended periods should periodically reevaluate the long–term usefulness of the drug for the individual patient (see DOSAGE AND ADMINISTRATION).

Pediatric (children and adolescents) — The efficacy of Prozac in children and adolescents was established in a 13–week, dose titration, clinical trial in patients with OCD, as defined in DSM–IV (see CLINICAL TRIALS).

Bulimia Nervosa

Prozac is indicated for the treatment of binge–eating and vomiting behaviors in patients with moderate to severe bulimia nervosa.

The efficacy of Prozac was established in 8– to 16–week trials for adult outpatients with moderate to severe bulimia nervosa, i.e., at least 3 bulimic episodes per week for 6 months (see CLINICAL TRIALS).

The efficacy of Prozac 60 mg/day in maintaining a response, in patients with bulimia who responded during an 8–week acute treatment phase while taking Prozac 60 mg/day and were then observed for relapse during a period of up to 52 weeks, was demonstrated in a placebo–controlled trial (see CLINICAL TRIALS). Nevertheless, the physician who elects to use Prozac for extended periods should periodically reevaluate the long–term usefulness of the drug for the individual patient (see DOSAGE AND ADMINISTRATION).

Panic Disorder

Prozac is indicated for the treatment of panic disorder, with or without agoraphobia, as defined in DSM–IV. Panic disorder is characterized by the occurrence of unexpected panic attacks, and associated concern about having additional attacks, worry about the implications or consequences of the attacks, and/or a significant change in behavior related to the attacks.

The efficacy of Prozac was established in two 12–week clinical trials in patients whose diagnoses corresponded to the DSM–IV category of panic disorder (see CLINICAL TRIALS).

Panic disorder (DSM–IV) is characterized by recurrent, unexpected panic attacks, i.e., a discrete period of intense fear or discomfort in which 4 or more of the following symptoms develop abruptly and reach a peak within 10 minutes: 1) palpitations, pounding heart, or accelerated heart rate; 2) sweating; 3) trembling or shaking; 4) sensations of shortness of breath or smothering; 5) feeling of choking; 6) chest pain or discomfort; 7) nausea or abdominal distress; 8) feeling dizzy, unsteady, lightheaded, or faint; 9) fear of losing control; 10) fear of dying; 11) paresthesias (numbness or tingling sensations); 12) chills or hot flashes.

The effectiveness of Prozac in long–term use, i.e., for more than 12 weeks, has not been established in placebo–controlled trials. Therefore, the physician who elects to use Prozac for extended periods should periodically reevaluate the long–term usefulness of the drug for the individual patient (see DOSAGE AND ADMINISTRATION).

CONTRAINDICATIONS

Prozac is contraindicated in patients known to be hypersensitive to it.

Monoamine oxidase inhibitors — There have been reports of serious, sometimes fatal, reactions (including hyperthermia, rigidity, myoclonus, autonomic instability with possible rapid fluctuations of vital signs, and mental status changes that include extreme agitation progressing to delirium and coma) in patients receiving fluoxetine in combination with a monoamine oxidase inhibitor (MAOI), and in patients who have recently discontinued fluoxetine and are then started on an MAOI. Some cases presented with features resembling neuroleptic malignant syndrome. Therefore, Prozac should not be used in combination with an MAOI, or within a minimum of 14 days of discontinuing therapy with an MAOI. Since fluoxetine and its major metabolite have very long elimination half–lives, at least 5 weeks [perhaps longer, especially if fluoxetine has been prescribed chronically and/or at higher doses (see Accumulation and slow elimination under CLINICAL PHARMACOLOGY)] should be allowed after stopping Prozac before starting an MAOI.

Pimozide — Concomitant use in patients taking pimozide is contraindicated (see PRECAUTIONS).

Thioridazine — Thioridazine should not be administered with Prozac or within a minimum of 5 weeks after Prozac has been discontinued (see WARNINGS).

WARNINGS

Clinical Worsening and Suicide Risk — Patients with major depressive disorder (MDD), both adult and pediatric, may experience worsening of their depression and/or the emergence of suicidal ideation and behavior (suicidality) or unusual changes in behavior, whether or not they are taking antidepressant medications, and this risk may persist until significant remission occurs. Suicide is a known risk of depression and certain other psychiatric disorders, and these disorders themselves are the strongest predictors of suicide. There has been a long–standing concern, however, that antidepressants may have a role in inducing worsening of depression and the emergence of suicidality in certain patients during the early phases of treatment. Pooled analyses of short–term placebo–controlled trials of antidepressant drugs (SSRIs and others) showed that these drugs increase the risk of suicidal thinking and behavior (suicidality) in children, adolescents, and young adults (ages 18–24) with major depressive disorder (MDD) and other psychiatric disorders. Short–term studies did not show an increase in the risk of suicidality with antidepressants compared to placebo in adults beyond age 24; there was a reduction with antidepressants compared to placebo in adults aged 65 and older.

The pooled analyses of placebo–controlled trials in children and adolescents with MDD, obsessive compulsive disorder (OCD), or other psychiatric disorders included a total of 24 short–term trials of 9 antidepressant drugs in over 4400 patients. The pooled analyses of placebo–controlled trials in adults with MDD or other psychiatric disorders included a total of 295 short–term trials (median duration of 2 months) of 11 antidepressant drugs in over 77,000 patients. There was considerable variation in risk of suicidality among drugs, but a tendency toward an increase in the younger patients for almost all drugs studied. There were differences in absolute risk of suicidality across the different indications, with the highest incidence in MDD. The risk differences (drug versus placebo), however, were relatively stable within age strata and across indications. These risk differences (drug–placebo difference in the number of cases of suicidality per 1000 patients treated) are provided in Table

No suicides occurred in any of the pediatric trials. There were suicides in the adult trials, but the number was not sufficient to reach any conclusion about drug effect on suicide.

It is unknown whether the suicidality risk extends to longer–term use, i.e., beyond several months. However, there is substantial evidence from placebo-controlled maintenance trials in adults with depression that the use of antidepressants can delay the recurrence of depression.

All patients being treated with antidepressants for any indication should be monitored appropriately and observed closely for clinical worsening, suicidality, and unusual changes in behavior, especially during the initial few months of a course of drug therapy, or at times of dose changes, either increases or decreases.

The following symptoms, anxiety, agitation, panic attacks, insomnia, irritability, hostility, aggressiveness, impulsivity, akathisia (psychomotor restlessness), hypomania, and mania, have been reported in adult and pediatric patients being treated with antidepressants for major depressive disorder as well as for other indications, both psychiatric and nonpsychiatric. Although a causal link between the emergence of such symptoms and either the worsening of depression and/or the emergence of suicidal impulses has not been established, there is concern that such symptoms may represent precursors to emerging suicidality.

Consideration should be given to changing the therapeutic regimen, including possibly discontinuing the medication, in patients whose depression is persistently worse, or who are experiencing emergent suicidality or symptoms that might be precursors to worsening depression or suicidality, especially if these symptoms are severe, abrupt in onset, or were not part of the patient’s presenting symptoms.

If the decision has been made to discontinue treatment, medication should be tapered, as rapidly as is feasible, but with recognition that abrupt discontinuation can be associated with certain symptoms (see PRECAUTIONS and DOSAGE AND ADMINISTRATION, Discontinuation of Treatment with Prozac, for a description of the risks of discontinuation of Prozac).

Families and caregivers of patients being treated with antidepressants for major depressive disorder or other indications, both psychiatric and nonpsychiatric, should be alerted about the need to monitor patients for the emergence of agitation, irritability, unusual changes in behavior, and the other symptoms described above, as well as the emergence of suicidality, and to report such symptoms immediately to health care providers. Such monitoring should include daily observation by families and caregivers. Prescriptions for Prozac should be written for the smallest quantity of capsules, or liquid consistent with good patient management, in order to reduce the risk of overdose.

It should be noted that Prozac is approved in the pediatric population only for major depressive disorder and obsessive compulsive disorder.

Screening Patients for Bipolar Disorder — A major depressive episode may be the initial presentation of bipolar disorder. It is generally believed (though not established in controlled trials) that treating such an episode with an antidepressant alone may increase the likelihood of precipitation of a mixed/manic episode in patients at risk for bipolar disorder. Whether any of the symptoms described above represent such a conversion is unknown. However, prior to initiating treatment with an antidepressant, patients with depressive symptoms should be adequately screened to determine if they are at risk for bipolar disorder; such screening should include a detailed psychiatric history, including a family history of suicide, bipolar disorder, and depression. It should be noted that Prozac is not approved for use in treating bipolar depression.

Rash and Possibly Allergic Events — In US fluoxetine clinical trials as of May 8, 1995, 7% of 10,782 patients developed various types of rashes and/or urticaria. Among the cases of rash and/or urticaria reported in premarketing clinical trials, almost a third were withdrawn from treatment because of the rash and/or systemic signs or symptoms associated with the rash. Clinical findings reported in association with rash include fever, leukocytosis, arthralgias, edema, carpal tunnel syndrome, respiratory distress, lymphadenopathy, proteinuria, and mild transaminase elevation. Most patients improved promptly with discontinuation of fluoxetine and/or adjunctive treatment with antihistamines or steroids, and all patients experiencing these events were reported to recover completely.

In premarketing clinical trials, 2 patients are known to have developed a serious cutaneous systemic illness. In neither patient was there an unequivocal diagnosis, but one was considered to have a leukocytoclastic vasculitis, and the other, a severe desquamating syndrome that was considered variously to be a vasculitis or erythema multiforme. Other patients have had systemic syndromes suggestive of serum sickness.

Since the introduction of Prozac, systemic events, possibly related to vasculitis and including lupus–like syndrome, have developed in patients with rash. Although these events are rare, they may be serious, involving the lung, kidney, or liver. Death has been reported to occur in association with these systemic events.

Anaphylactoid events, including bronchospasm, angioedema, laryngospasm, and urticaria alone and in combination, have been reported.

Pulmonary events, including inflammatory processes of varying histopathology and/or fibrosis, have been reported rarely. These events have occurred with dyspnea as the only preceding symptom.

Whether these systemic events and rash have a common underlying cause or are due to different etiologies or pathogenic processes is not known. Furthermore, a specific underlying immunologic basis for these events has not been identified. Upon the appearance of rash or of other possibly allergic phenomena for which an alternative etiology cannot be identified, Prozac should be discontinued.

Serotonin Syndrome — The development of a potentially life–threatening serotonin syndrome may occur with SNRIs and SSRIs, including Prozac treatment, particularly with concomitant use of serotonergic drugs (including triptans) and with drugs which impair metabolism of serotonin (including MAOIs). Serotonin syndrome symptoms may include mental status changes (e.g., agitation, hallucinations, coma), autonomic instability (e.g., tachycardia, labile blood pressure, hyperthermia), neuromuscular aberrations (e.g., hyperreflexia, incoordination) and/or gastrointestinal symptoms (e.g., nausea, vomiting, diarrhea).

The concomitant use of Prozac with MAOIs intended to treat depression is contraindicated (see CONTRAINDICATIONS and Drug Interactions under PRECAUTIONS).

If concomitant treatment Prozac with a 5–hydroxytryptamine receptor agonist (triptan) is clinically warranted, careful observation of the patient is advised, particularly during treatment initiation and dose increases (see Drug Interactions under PRECAUTIONS).

The concomitant use of Prozac with serotonin precursors (such as tryptophan) is not recommended (see Drug Interactions under PRECAUTIONS).

Potential Interaction with Thioridazine — In a study of 19 healthy male subjects, which included 6 slow and 13 rapid hydroxylators of debrisoquin, a single 25–mg oral dose of thioridazine produced a 2.4–fold higher Cmax and a 4.5–fold higher AUC for thioridazine in the slow hydroxylators compared with the rapid hydroxylators. The rate of debrisoquin hydroxylation is felt to depend on the level of CYP2D6 isozyme activity. Thus, this study suggests that drugs which inhibit CYP2D6, such as certain SSRIs, including fluoxetine, will produce elevated plasma levels of thioridazine (see PRECAUTIONS).

Thioridazine administration produces a dose–related prolongation of the QTc interval, which is associated with serious ventricular arrhythmias, such as torsades de pointes–type arrhythmias, and sudden death. This risk is expected to increase with fluoxetine–induced inhibition of thioridazine metabolism (see CONTRAINDICATIONS).

PRECAUTIONS

PRECAUTIONSGeneral

Abnormal Bleeding — SSRIs and SNRIs, including fluoxetine, may increase the risk of bleeding events. Concomitant use of aspirin, nonsteroidal anti-inflammatory drugs, warfarin, and other anti-coagulants may add to this risk. Case reports and epidemiological studies (case-control and cohort design) have demonstrated an association between use of drugs that interfere with serotonin reuptake and the occurrence of gastrointestinal bleeding. Bleeding events related to SSRIs and SNRIs use have ranged from ecchymoses, hematomas, epistaxis, and petechiae to life-threatening hemorrhages.

Patients should be cautioned about the risk of bleeding associated with the concomitant use of fluoxetine and NSAIDs, aspirin, or other drugs that affect coagulation (see Drug Interactions).

Anxiety and Insomnia — In US placebo–controlled clinical trials for major depressive disorder, 12% to 16% of patients treated with Prozac and 7% to 9% of patients treated with placebo reported anxiety, nervousness, or insomnia.

In US placebo–controlled clinical trials for OCD, insomnia was reported in 28% of patients treated with Prozac and in 22% of patients treated with placebo. Anxiety was reported in 14% of patients treated with Prozac and in 7% of patients treated with placebo.

In US placebo–controlled clinical trials for bulimia nervosa, insomnia was reported in 33% of patients treated with Prozac 60 mg, and 13% of patients treated with placebo. Anxiety and nervousness were reported, respectively, in 15% and 11% of patients treated with Prozac 60 mg and in 9% and 5% of patients treated with placebo.

Among the most common adverse events associated with discontinuation (incidence at least twice that for placebo and at least 1% for Prozac in clinical trials collecting only a primary event associated with discontinuation) in US placebo–controlled fluoxetine clinical trials were anxiety (2% in OCD), insomnia (1% in combined indications and 2% in bulimia), and nervousness (1% in major depressive disorder) (see Table 4).

Altered Appetite and Weight — Significant weight loss, especially in underweight depressed or bulimic patients may be an undesirable result of treatment with Prozac.

In US placebo–controlled clinical trials for major depressive disorder, 11% of patients treated with Prozac and 2% of patients treated with placebo reported anorexia (decreased appetite). Weight loss was reported in 1.4% of patients treated with Prozac and in 0.5% of patients treated with placebo. However, only rarely have patients discontinued treatment with Prozac because of anorexia or weight loss (see also Pediatric Use under PRECAUTIONS).

In US placebo–controlled clinical trials for OCD, 17% of patients treated with Prozac and 10% of patients treated with placebo reported anorexia (decreased appetite). One patient discontinued treatment with Prozac because of anorexia (see also Pediatric Use under PRECAUTIONS).

In US placebo–controlled clinical trials for bulimia nervosa, 8% of patients treated with Prozac 60 mg and 4% of patients treated with placebo reported anorexia (decreased appetite). Patients treated with Prozac 60 mg on average lost 0.45 kg compared with a gain of 0.16 kg by patients treated with placebo in the 16–week double–blind trial. Weight change should be monitored during therapy.

Activation of Mania/Hypomania — In US placebo–controlled clinical trials for major depressive disorder, mania/hypomania was reported in 0.1% of patients treated with Prozac and 0.1% of patients treated with placebo. Activation of mania/hypomania has also been reported in a small proportion of patients with Major Affective Disorder treated with other marketed drugs effective in the treatment of major depressive disorder (see also Pediatric Use under PRECAUTIONS).

In US placebo–controlled clinical trials for OCD, mania/hypomania was reported in 0.8% of patients treated with Prozac and no patients treated with placebo. No patients reported mania/hypomania in US placebo–controlled clinical trials for bulimia. In all US Prozac clinical trials as of May 8, 1995, 0.7% of 10,782 patients reported mania/hypomania (see also Pediatric Use under PRECAUTIONS).

Hyponatremia — Hyponatremia may occur as a result of treatment with SSRIs and SNRIs, including Prozac. In many cases, this hyponatremia appears to be the result of the syndrome of inappropriate antidiuretic hormone secretion (SIADH). Cases with serum sodium lower than 110 mmol/L have been reported and appeared to be reversible when Prozac was discontinued. Elderly patients may be at greater risk of developing hyponatremia with SSRIs and SNRIs. Also, patients taking diuretics or who are otherwise volume depleted may be at greater risk (see Geriatric Use). Discontinuation of Prozac should be considered in patients with symptomatic hyponatremia and appropriate medical intervention should be instituted.

Signs and symptoms of hyponatremia include headache, difficulty concentrating, memory impairment, confusion, weakness, and unsteadiness, which may lead to falls. More severe and/or acute cases have been associated with hallucination, syncope, seizure, coma, respiratory arrest, and death.

Seizures — In US placebo–controlled clinical trials for major depressive disorder, convulsions (or events described as possibly having been seizures) were reported in 0.1% of patients treated with Prozac and 0.2% of patients treated with placebo. No patients reported convulsions in US placebo–controlled clinical trials for either OCD or bulimia. In all US Prozac clinical trials as of May 8, 1995, 0.2% of 10,782 patients reported convulsions. The percentage appears to be similar to that associated with other marketed drugs effective in the treatment of major depressive disorder. Prozac should be introduced with care in patients with a history of seizures.

The Long Elimination Half–Lives of Fluoxetine and its Metabolites — Because of the long elimination half–lives of the parent drug and its major active metabolite, changes in dose will not be fully reflected in plasma for several weeks, affecting both strategies for titration to final dose and withdrawal from treatment (see CLINICAL PHARMACOLOGY and DOSAGE AND ADMINISTRATION).

Use in Patients with Concomitant Illness — Clinical experience with Prozac in patients with concomitant systemic illness is limited. Caution is advisable in using Prozac in patients with diseases or conditions that could affect metabolism or hemodynamic responses.

Fluoxetine has not been evaluated or used to any appreciable extent in patients with a recent history of myocardial infarction or unstable heart disease. Patients with these diagnoses were systematically excluded from clinical studies during the product’s premarket testing. However, the electrocardiograms of 312 patients who received Prozac in double–blind trials were retrospectively evaluated; no conduction abnormalities that resulted in heart block were observed. The mean heart rate was reduced by approximately 3 beats/min.

In subjects with cirrhosis of the liver, the clearances of fluoxetine and its active metabolite, norfluoxetine, were decreased, thus increasing the elimination half–lives of these substances. A lower or less frequent dose should be used in patients with cirrhosis.

Studies in depressed patients on dialysis did not reveal excessive accumulation of fluoxetine or norfluoxetine in plasma (see Renal disease under CLINICAL PHARMACOLOGY). Use of a lower or less frequent dose for renally impaired patients is not routinely necessary (see DOSAGE AND ADMINISTRATION).

In patients with diabetes, Prozac may alter glycemic control. Hypoglycemia has occurred during therapy with Prozac, and hyperglycemia has developed following discontinuation of the drug. As is true with many other types of medication when taken concurrently by patients with diabetes, insulin and/or oral hypoglycemic dosage may need to be adjusted when therapy with Prozac is instituted or discontinued.

Interference with Cognitive and Motor Performance — Any psychoactive drug may impair judgment, thinking, or motor skills, and patients should be cautioned about operating hazardous machinery, including automobiles, until they are reasonably certain that the drug treatment does not affect them adversely.

Discontinuation of Treatment with Prozac — During marketing of Prozac and other SSRIs and SNRIs (serotonin and norepinephrine reuptake inhibitors), there have been spontaneous reports of adverse events occurring upon discontinuation of these drugs, particularly when abrupt, including the following: dysphoric mood, irritability, agitation, dizziness, sensory disturbances (e.g., paresthesias such as electric shock sensations), anxiety, confusion, headache, lethargy, emotional lability, insomnia, and hypomania. While these events are generally self–limiting, there have been reports of serious discontinuation symptoms. Patients should be monitored for these symptoms when discontinuing treatment with Prozac. A gradual reduction in the dose rather than abrupt cessation is recommended whenever possible. If intolerable symptoms occur following a decrease in the dose or upon discontinuation of treatment, then resuming the previously prescribed dose may be considered. Subsequently, the physician may continue decreasing the dose but at a more gradual rate. Plasma fluoxetine and norfluoxetine concentration decrease gradually at the conclusion of therapy, which may minimize the risk of discontinuation symptoms with this drug (see DOSAGE AND ADMINISTRATION).

Information for Patients

Prescribers or other health professionals should inform patients, their families, and their caregivers about the benefits and risks associated with treatment with Prozac and should counsel them in its appropriate use. A patient Medication Guide about“Antidepressant Medicines, Depression and other Serious Mental Illnesses, and Suicidal Thoughts or Actions” is available for Prozac. The prescriber or health professional should instruct patients, their families, and their caregivers to read the Medication Guide and should assist them in understanding its contents. Patients should be given the opportunity to discuss the contents of the Medication Guide and to obtain answers to any questions they may have. The complete text of the Medication Guide is reprinted at the end of this document.

Patients should be advised of the following issues and asked to alert their prescriber if these occur while taking Prozac.

Clinical Worsening and Suicide Risk — Patients, their families, and their caregivers should be encouraged to be alert to the emergence of anxiety, agitation, panic attacks, insomnia, irritability, hostility, aggressiveness, impulsivity, akathisia (psychomotor restlessness), hypomania, mania, other unusual changes in behavior, worsening of depression, and suicidal ideation, especially early during antidepressant treatment and when the dose is adjusted up or down. Families and caregivers of patients should be advised to look for the emergence of such symptoms on a day–to–day basis, since changes may be abrupt. Such symptoms should be reported to the patient’s prescriber or health professional, especially if they are severe, abrupt in onset, or were not part of the patient’s presenting symptoms. Symptoms such as these may be associated with an increased risk for suicidal thinking and behavior and indicate a need for very close monitoring and possibly changes in the medication.

Serotonin Syndrome — Patients should be cautioned about the risk of serotonin syndrome with the concomitant use of Prozac and triptans, tramadol or other serotonergic agents.

Because Prozac may impair judgment, thinking, or motor skills, patients should be advised to avoid driving a car or operating hazardous machinery until they are reasonably certain that their performance is not affected.

Patients should be advised to inform their physician if they are taking or plan to take any prescription or over–the–counter drugs, or alcohol.

Abnormal Bleeding- Patients should be cautioned about the concomitant use of fluoxetine and NSAIDs, aspirin, warfarin, or other drugs that affect coagulation since combined use of psychotropic drugs that interfere with serotonin reuptake and these agents have been associated with an increased risk of bleeding (see PRECAUTIONS, Abnormal Bleeding).

Patients should be advised to notify their physician if they become pregnant or intend to become pregnant during therapy.

Patients should be advised to notify their physician if they are breast–feeding an infant.

Patients should be advised to notify their physician if they develop a rash or hives.

Laboratory Tests

There are no specific laboratory tests recommended.

Drug Interactions

As with all drugs, the potential for interaction by a variety of mechanisms (e.g., pharmacodynamic, pharmacokinetic drug inhibition or enhancement, etc.) is a possibility (see Accumulation and slow elimination under CLINICAL PHARMACOLOGY).

Drugs metabolized by CYP2D6 — Fluoxetine inhibits the activity of CYP2D6, and may make individuals with normal CYP2D6 metabolic activity resemble a poor metabolizer. Coadministration of fluoxetine with other drugs that are metabolized by CYP2D6, including certain antidepressants (e.g., TCAs), antipsychotics (e.g., phenothiazines and most atypicals), and antiarrhythmics (e.g., propafenone, flecainide, and others) should be approached with caution. Therapy with medications that are predominantly metabolized by the CYP2D6 system and that have a relatively narrow therapeutic index (see list below) should be initiated at the low end of the dose range if a patient is receiving fluoxetine concurrently or has taken it in the previous 5 weeks. Thus, his/her dosing requirements resemble those of poor metabolizers. If fluoxetine is added to the treatment regimen of a patient already receiving a drug metabolized by CYP2D6, the need for decreased dose of the original medication should be considered. Drugs with a narrow therapeutic index represent the greatest concern (e.g., flecainide, propafenone, vinblastine, and TCAs). Due to the risk of serious ventricular arrhythmias and sudden death potentially associated with elevated plasma levels of thioridazine, thioridazine should not be administered with fluoxetine or within a minimum of 5 weeks after fluoxetine has been discontinued (see CONTRAINDICATIONS and WARNINGS).

Drugs metabolized by CYP3A4 — In an in vivo interaction study involving coadministration of fluoxetine with single doses of terfenadine (a CYP3A4 substrate), no increase in plasma terfenadine concentrations occurred with concomitant fluoxetine. In addition, in vitro studies have shown ketoconazole, a potent inhibitor of CYP3A4 activity, to be at least 100 times more potent than fluoxetine or norfluoxetine as an inhibitor of the metabolism of several substrates for this enzyme, including astemizole, cisapride, and midazolam. These data indicate that fluoxetine’s extent of inhibition of CYP3A4 activity is not likely to be of clinical significance.

CNS active drugs — The risk of using Prozac in combination with other CNS active drugs has not been systematically evaluated. Nonetheless, caution is advised if the concomitant administration of Prozac and such drugs is required. In evaluating individual cases, consideration should be given to using lower initial doses of the concomitantly administered drugs, using conservative titration schedules, and monitoring of clinical status (see Accumulation and slow elimination under CLINICAL PHARMACOLOGY).

Anticonvulsants — Patients on stable doses of phenytoin and carbamazepine have developed elevated plasma anticonvulsant concentrations and clinical anticonvulsant toxicity following initiation of concomitant fluoxetine treatment.

Antipsychotics — Some clinical data suggests a possible pharmacodynamic and/or pharmacokinetic interaction between SSRIs and antipsychotics. Elevation of blood levels of haloperidol and clozapine has been observed in patients receiving concomitant fluoxetine. Clinical studies of pimozide with other antidepressants demonstrate an increase in drug interaction or QTc prolongation. While a specific study with pimozide and fluoxetine has not been conducted, the potential for drug interactions or QTc prolongation warrants restricting the concurrent use of pimozide and Prozac. Concomitant use of Prozac and pimozide is contraindicated (see CONTRAINDICATIONS). For thioridazine, see CONTRAINDICATIONS and WARNINGS.

Benzodiazepines — The half–life of concurrently administered diazepam may be prolonged in some patients (see Accumulation and slow elimination under CLINICAL PHARMACOLOGY). Coadministration of alprazolam and fluoxetine has resulted in increased alprazolam plasma concentrations and in further psychomotor performance decrement due to increased alprazolam levels.

Lithium — There have been reports of both increased and decreased lithium levels when lithium was used concomitantly with fluoxetine. Cases of lithium toxicity and increased serotonergic effects have been reported. Lithium levels should be monitored when these drugs are administered concomitantly.

Tryptophan — Five patients receiving Prozac in combination with tryptophan experienced adverse reactions, including agitation, restlessness, and gastrointestinal distress.

Monoamine oxidase inhibitors — See CONTRAINDICATIONS.

Other drugs effective in the treatment of major depressive disorder — In 2 studies, previously stable plasma levels of imipramine and desipramine have increased greater than 2– to 10–fold when fluoxetine has been administered in combination. This influence may persist for 3 weeks or longer after fluoxetine is discontinued. Thus, the dose of TCA may need to be reduced and plasma TCA concentrations may need to be monitored temporarily when fluoxetine is coadministered or has been recently discontinued (see Accumulation and slow elimination under CLINICAL PHARMACOLOGY, and Drugs metabolized by CYP2D6 under Drug Interactions).

Serotonergic drugs — Based on the mechanism of action of SNRIs and SSRIs, including Prozac, and the potential for serotonin syndrome, caution is advised when Prozac is coadministered with other drugs that may affect the serotonergic neurotransmitter systems, such as triptans, linezolid (an antibiotic which is a reversible non–selective MAOI), lithium, tramadol, or St. John’s Wort (see Serotonin Syndrome under WARNINGS). The concomitant use of Prozac with other SSRIs, SNRIs or tryptophan is not recommended (see Tryptophan).

Triptans — There have been rare postmarketing reports of serotonin syndrome with use of an SSRI and a triptan. If concomitant treatment of Prozac with a triptan is clinically warranted, careful observation of the patient is advised, particularly during treatment initiation and dose increases (see Serotonin Syndrome under WARNINGS).

Potential effects of coadministration of drugs tightly bound to plasma proteins — Because fluoxetine is tightly bound to plasma protein, the administration of fluoxetine to a patient taking another drug that is tightly bound to protein (e.g., Coumadin, digitoxin) may cause a shift in plasma concentrations potentially resulting in an adverse effect. Conversely, adverse effects may result from displacement of protein–bound fluoxetine by other tightly–bound drugs (see Accumulation and slow elimination under CLINICAL PHARMACOLOGY).

Drugs that interfere with hemostasis (e.g., NSAIDs, Aspirin, Warfarin) — Serotonin release by platelets plays an important role in hemostasis. Epidemiological studies of the case–control and cohort design that have demonstrated an association between use of psychotropic drugs that interfere with serotonin reuptake and the occurrence of upper gastrointestinal bleeding have also shown that concurrent use of an NSAID or aspirin may potentiate this risk of bleeding. Altered anticoagulant effects, including increased bleeding, have been reported when SSRIs or SNRIs are coadministered with warfarin. Patients receiving warfarin therapy should be carefully monitored when fluoxetine is initiated or discontinued.

Electroconvulsive therapy (ECT) — There are no clinical studies establishing the benefit of the combined use of ECT and fluoxetine. There have been rare reports of prolonged seizures in patients on fluoxetine receiving ECT treatment.

Carcinogenesis, Mutagenesis, Impairment of Fertility

There is no evidence of carcinogenicity or mutagenicity from in vitro or animal studies. Impairment of fertility in adult animals at doses up to 12.5 mg/kg/day (approximately 1.5 times the MRHD on a mg/m^2 basis) was not observed.

Carcinogenicity — The dietary administration of fluoxetine to rats and mice for 2 years at doses of up to 10 and 12 mg/kg/day, respectively [approximately 1.2 and 0.7 times, respectively, the maximum recommended human dose (MRHD) of 80 mg on a mg/m^2 basis], produced no evidence of carcinogenicity.

Mutagenicity — Fluoxetine and norfluoxetine have been shown to have no genotoxic effects based on the following assays: bacterial mutation assay, DNA repair assay in cultured rat hepatocytes, mouse lymphoma assay, and in vivo sister chromatid exchange assay in Chinese hamster bone marrow cells.

Impairment of fertility — Two fertility studies conducted in adult rats at doses of up to 7.5 and 12.5 mg/kg/day (approximately 0.9 and 1.5 times the MRHD on a mg/m^2 basis) indicated that fluoxetine had no adverse effects on fertility (see Pediatric Use).

Pregnancy Pregnancy Category C

In embryo–fetal development studies in rats and rabbits, there was no evidence of teratogenicity following administration of up to 12.5 and 15 mg/kg/day, respectively (1.5 and 3.6 times, respectively, the MRHD of 80 mg on a mg/m^2 basis) throughout organogenesis. However, in rat reproduction studies, an increase in stillborn pups, a decrease in pup weight, and an increase in pup deaths during the first 7 days postpartum occurred following maternal exposure to 12 mg/kg/day (1.5 times the MRHD on a mg/m^2 basis) during gestation or 7.5 mg/kg/day (0.9 times the MRHD on a mg/m^2 basis) during gestation and lactation. There was no evidence of developmental neurotoxicity in the surviving offspring of rats treated with 12 mg/kg/day during gestation. The no–effect dose for rat pup mortality was 5 mg/kg/day (0.6 times the MRHD on a mg/m^2 basis). Prozac should be used during pregnancy only if the potential benefit justifies the potential risk to the fetus.

Nonteratogenic Effects

Neonates exposed to Prozac and other SSRIs or serotonin and norepinephrine reuptake inhibitors (SNRIs), late in the third trimester have developed complications requiring prolonged hospitalization, respiratory support, and tube feeding. Such complications can arise immediately upon delivery. Reported clinical findings have included respiratory distress, cyanosis, apnea, seizures, temperature instability, feeding difficulty, vomiting, hypoglycemia, hypotonia, hypertonia, hyperreflexia, tremor, jitteriness, irritability, and constant crying. These features are consistent with either a direct toxic effect of SSRIs and SNRIs or, possibly, a drug discontinuation syndrome. It should be noted that, in some cases, the clinical picture is consistent with serotonin syndrome (see Monoamine oxidase inhibitors under CONTRAINDICATIONS).

Infants exposed to SSRIs in late pregnancy may have an increased risk for persistent pulmonary hypertension of the newborn (PPHN). PPHN occurs in 1–2 per 1000 live births in the general population and is associated with substantial neonatal morbidity and mortality. In a retrospective case–control study of 377 women whose infants were born with PPHN and 836 women whose infants were born healthy, the risk for developing PPHN was approximately six–fold higher for infants exposed to SSRIs after the 20th week of gestation compared to infants who had not been exposed to antidepressants during pregnancy. There is currently no corroborative evidence regarding the risk for PPHN following exposure to SSRIs in pregnancy; this is the first study that has investigated the potential risk. The study did not include enough cases with exposure to individual SSRIs to determine if all SSRIs posed similar levels of PPHN risk.

When treating a pregnant woman with Prozac during the third trimester, the physician should carefully consider both the potential risks and benefits of treatment (see DOSAGE AND ADMINISTRATION). Physicians should note that in a prospective longitudinal study of 201 women with a history of major depression who were euthymic at the beginning of pregnancy, women who discontinued antidepressant medication during pregnancy were more likely to experience a relapse of major depression than women who continued antidepressant medication.

Labor and Delivery

The effect of Prozac on labor and delivery in humans is unknown. However, because fluoxetine crosses the placenta and because of the possibility that fluoxetine may have adverse effects on the newborn, fluoxetine should be used during labor and delivery only if the potential benefit justifies the potential risk to the fetus.

Nursing Mothers

Because Prozac is excreted in human milk, nursing while on Prozac is not recommended. In one breast–milk sample, the concentration of fluoxetine plus norfluoxetine was 70.4 ng/mL. The concentration in the mother’s plasma was 295.0 ng/mL. No adverse effects on the infant were reported. In another case, an infant nursed by a mother on Prozac developed crying, sleep disturbance, vomiting, and watery stools. The infant’s plasma drug levels were 340 ng/mL of fluoxetine and 208 ng/mL of norfluoxetine on the second day of feeding.

Pediatric Use

The efficacy of Prozac for the treatment of major depressive disorder was demonstrated in two 8– to 9–week placebo–controlled clinical trials with 315 pediatric outpatients ages 8 to ≤18 (see CLINICAL TRIALS).

ADVERSE REACTIONS

Multiple doses of Prozac had been administered to 10,782 patients with various diagnoses in US clinical trials as of May 8, 1995. In addition, there have been 425 patients administered Prozac in panic clinical trials. Adverse events were recorded by clinical investigators using descriptive terminology of their own choosing. Consequently, it is not possible to provide a meaningful estimate of the proportion of individuals experiencing adverse events without first grouping similar types of events into a limited (i.e., reduced) number of standardized event categories.

In the tables and tabulations that follow, COSTART Dictionary terminology has been used to classify reported adverse events. The stated frequencies represent the proportion of individuals who experienced, at least once, a treatment–emergent adverse event of the type listed. An event was considered treatment–emergent if it occurred for the first time or worsened while receiving therapy following baseline evaluation. It is important to emphasize that events reported during therapy were not necessarily caused by it.

The prescriber should be aware that the figures in the tables and tabulations cannot be used to predict the incidence of side effects in the course of usual medical practice where patient characteristics and other factors differ from those that prevailed in the clinical trials. Similarly, the cited frequencies cannot be compared with figures obtained from other clinical investigations involving different treatments, uses, and investigators. The cited figures, however, do provide the prescribing physician with some basis for estimating the relative contribution of drug and nondrug factors to the side effect incidence rate in the population studied.

Incidence in major depressive disorder, OCD, bulimia, and panic disorder placebo–controlled clinical trials (excluding data from extensions of trials) — Table 2 enumerates the most common treatment–emergent adverse events associated with the use of Prozac (incidence of at least 5% for Prozac and at least twice that for placebo within at least 1 of the indications) for the treatment of major depressive disorder, OCD, and bulimia in US controlled clinical trials and panic disorder in US plus non–US controlled trials. Table 3 enumerates treatment–emergent adverse events that occurred in 2% or more patients treated with Prozac and with incidence greater than placebo who participated in US major depressive disorder, OCD, and bulimia controlled clinical trials and US plus non–US panic disorder controlled clinical trials. Table 3 provides combined data for the pool of studies that are provided separately by indication in Table 2.

Other adverse events in pediatric patients (children and adolescents) — Treatment–emergent adverse events were collected in 322 pediatric patients (180 fluoxetine–treated, 142 placebo–treated). The overall profile of adverse events was generally similar to that seen in adult studies, as shown in Tables 2 and 3. However, the following adverse events (excluding those which appear in the body or footnotes of Tables 2 and 3 and those for which the COSTART terms were uninformative or misleading) were reported at an incidence of at least 2% for fluoxetine and greater than placebo: thirst, hyperkinesia, agitation, personality disorder, epistaxis, urinary frequency, and menorrhagia.

The most common adverse event (incidence at least 1% for fluoxetine and greater than placebo) associated with discontinuation in 3 pediatric placebo–controlled trials (N=418 randomized; 228 fluoxetine–treated; 190 placebo–treated) was mania/hypomania (1.8% for fluoxetine–treated, 0% for placebo–treated). In these clinical trials, only a primary event associated with discontinuation was collected.

Events observed in Prozac Weekly clinical trials — Treatment–emergent adverse events in clinical trials with Prozac Weekly were similar to the adverse events reported by patients in clinical trials with Prozac daily. In a placebo–controlled clinical trial, more patients taking Prozac Weekly reported diarrhea than patients taking placebo (10% versus 3%, respectively) or taking Prozac 20 mg daily (10% versus 5%, respectively).

OVERDOSAGE

OVERDOSAGEHuman Experience

Worldwide exposure to fluoxetine hydrochloride is estimated to be over 38 million patients (circa 1999). Of the 1578 cases of overdose involving fluoxetine hydrochloride, alone or with other drugs, reported from this population, there were 195 deaths.

Among 633 adult patients who overdosed on fluoxetine hydrochloride alone, 34 resulted in a fatal outcome, 378 completely recovered, and 15 patients experienced sequelae after overdosage, including abnormal accommodation, abnormal gait, confusion, unresponsiveness, nervousness, pulmonary dysfunction, vertigo, tremor, elevated blood pressure, impotence, movement disorder, and hypomania. The remaining 206 patients had an unknown outcome. The most common signs and symptoms associated with non–fatal overdosage were seizures, somnolence, nausea, tachycardia, and vomiting. The largest known ingestion of fluoxetine hydrochloride in adult patients was 8 grams in a patient who took fluoxetine alone and who subsequently recovered. However, in an adult patient who took fluoxetine alone, an ingestion as low as 520 mg has been associated with lethal outcome, but causality has not been established.

Among pediatric patients (ages 3 months to 17 years), there were 156 cases of overdose involving fluoxetine alone or in combination with other drugs. Six patients died, 127 patients completely recovered, 1 patient experienced renal failure, and 22 patients had an unknown outcome. One of the six fatalities was a 9–year–old boy who had a history of OCD, Tourette’s syndrome with tics, attention deficit disorder, and fetal alcohol syndrome. He had been receiving 100 mg of fluoxetine daily for 6 months in addition to clonidine, methylphenidate, and promethazine. Mixed–drug ingestion or other methods of suicide complicated all 6 overdoses in children that resulted in fatalities. The largest ingestion in pediatric patients was 3 grams which was nonlethal.

Other important adverse events reported with fluoxetine overdose (single or multiple drugs) include coma, delirium, ECG abnormalities (such as QT interval prolongation and ventricular tachycardia, including torsades de pointes–type arrhythmias), hypotension, mania, neuroleptic malignant syndrome–like events, pyrexia, stupor, and syncope.

Animal Experience

Studies in animals do not provide precise or necessarily valid information about the treatment of human overdose. However, animal experiments can provide useful insights into possible treatment strategies.

The oral median lethal dose in rats and mice was found to be 452 and 248 mg/kg, respectively. Acute high oral doses produced hyperirritability and convulsions in several animal species.

Among 6 dogs purposely overdosed with oral fluoxetine, 5 experienced grand mal seizures. Seizures stopped immediately upon the bolus intravenous administration of a standard veterinary dose of diazepam. In this short–term study, the lowest plasma concentration at which a seizure occurred was only twice the maximum plasma concentration seen in humans taking 80 mg/day, chronically.

In a separate single–dose study, the ECG of dogs given high doses did not reveal prolongation of the PR, QRS, or QT intervals. Tachycardia and an increase in blood pressure were observed. Consequently, the value of the ECG in predicting cardiac toxicity is unknown. Nonetheless, the ECG should ordinarily be monitored in cases of human overdose (see Management of Overdose).

Management of Overdose

Treatment should consist of those general measures employed in the management of overdosage with any drug effective in the treatment of major depressive disorder.

Ensure an adequate airway, oxygenation, and ventilation. Monitor cardiac rhythm and vital signs. General supportive and symptomatic measures are also recommended. Induction of emesis is not recommended. Gastric lavage with a large–bore orogastric tube with appropriate airway protection, if needed, may be indicated if performed soon after ingestion, or in symptomatic patients.

Activated charcoal should be administered. Due to the large volume of distribution of this drug, forced diuresis, dialysis, hemoperfusion, and exchange transfusion are unlikely to be of benefit. No specific antidotes for fluoxetine are known.

A specific caution involves patients who are taking or have recently taken fluoxetine and might ingest excessive quantities of a TCA. In such a case, accumulation of the parent tricyclic and/or an active metabolite may increase the possibility of clinically significant sequelae and extend the time needed for close medical observation (see Other drugs effective in the treatment of major depressive disorder under PRECAUTIONS).

Based on experience in animals, which may not be relevant to humans, fluoxetine–induced seizures that fail to remit spontaneously may respond to diazepam.

In managing overdosage, consider the possibility of multiple drug involvement. The physician should consider contacting a poison control center for additional information on the treatment of any overdose. Telephone numbers for certified poison control centers are listed in the Physicians’ Desk Reference (PDR).

DOSAGE AND ADMINISTRATIONMajor Depressive Disorder Initial Treatment

Adult — In controlled trials used to support the efficacy of fluoxetine, patients were administered morning doses ranging from 20 to 80 mg/day. Studies comparing fluoxetine 20, 40, and 60 mg/day to placebo indicate that 20 mg/day is sufficient to obtain a satisfactory response in major depressive disorder in most cases. Consequently, a dose of 20 mg/day, administered in the morning, is recommended as the initial dose.

A dose increase may be considered after several weeks if insufficient clinical improvement is observed. Doses above 20 mg/day may be administered on a once–a–day (morning) or BID schedule (i.e., morning and noon) and should not exceed a maximum dose of 80 mg/day.

Pediatric (children and adolescents) — In the short–term (8 to 9 week) controlled clinical trials of fluoxetine supporting its effectiveness in the treatment of major depressive disorder, patients were administered fluoxetine doses of 10 to 20 mg/day (see CLINICAL TRIALS). Treatment should be initiated with a dose of 10 or 20 mg/day. After 1 week at 10 mg/day, the dose should be increased to 20 mg/day.

However, due to higher plasma levels in lower weight children, the starting and target dose in this group may be 10 mg/day. A dose increase to 20 mg/day may be considered after several weeks if insufficient clinical improvement is observed.

All patients — As with other drugs effective in the treatment of major depressive disorder, the full effect may be delayed until 4 weeks of treatment or longer.

As with many other medications, a lower or less frequent dosage should be used in patients with hepatic impairment. A lower or less frequent dosage should also be considered for the elderly (see Geriatric Use under PRECAUTIONS), and for patients with concurrent disease or on multiple concomitant medications. Dosage adjustments for renal impairment are not routinely necessary (see Liver disease and Renal disease under CLINICAL PHARMACOLOGY, and Use in Patients with Concomitant Illness under PRECAUTIONS).

Maintenance/Continuation/Extended Treatment

It is generally agreed that acute episodes of major depressive disorder require several months or longer of sustained pharmacologic therapy. Whether the dose needed to induce remission is identical to the dose needed to maintain and/or sustain euthymia is unknown.

Daily Dosing

Systematic evaluation of Prozac in adult patients has shown that its efficacy in major depressive disorder is maintained for periods of up to 38 weeks following 12 weeks of open–label acute treatment (50 weeks total) at a dose of 20 mg/day (see CLINICAL TRIALS).

Weekly Dosing

Systematic evaluation of Prozac Weekly in adult patients has shown that its efficacy in major depressive disorder is maintained for periods of up to 25 weeks with once–weekly dosing following 13 weeks of open–label treatment with Prozac 20 mg once daily. However, therapeutic equivalence of Prozac Weekly given on a once–weekly basis with Prozac 20 mg given daily for delaying time to relapse has not been established (see CLINICAL TRIALS).

Weekly dosing with Prozac Weekly capsules is recommended to be initiated 7 days after the last daily dose of Prozac 20 mg (see Weekly dosing under CLINICAL PHARMACOLOGY).

If satisfactory response is not maintained with Prozac Weekly, consider reestablishing a daily dosing regimen (see CLINICAL TRIALS).

Switching Patients to a Tricyclic Antidepressant (TCA)

Dosage of a TCA may need to be reduced, and plasma TCA concentrations may need to be monitored temporarily when fluoxetine is coadministered or has been recently discontinued (see Other drugs effective in the treatment of major depressive disorder under PRECAUTIONS, Drug Interactions).

Switching Patients to or from a Monoamine Oxidase Inhibitor (MAOI)

At least 14 days should elapse between discontinuation of an MAOI and initiation of therapy with Prozac. In addition, at least 5 weeks, perhaps longer, should be allowed after stopping Prozac before starting an MAOI (see CONTRAINDICATIONS and PRECAUTIONS).

Obsessive Compulsive Disorder Initial Treatment

Adult — In the controlled clinical trials of fluoxetine supporting its effectiveness in the treatment of OCD, patients were administered fixed daily doses of 20, 40, or 60 mg of fluoxetine or placebo (see CLINICAL TRIALS). In 1 of these studies, no dose–response relationship for effectiveness was demonstrated. Consequently, a dose of 20 mg/day, administered in the morning, is recommended as the initial dose. Since there was a suggestion of a possible dose–response relationship for effectiveness in the second study, a dose increase may be considered after several weeks if insufficient clinical improvement is observed. The full therapeutic effect may be delayed until 5 weeks of treatment or longer.

Doses above 20 mg/day may be administered on a once–a–day (i.e., morning) or BID schedule (i.e., morning and noon). A dose range of 20 to 60 mg/day is recommended; however, doses of up to 80 mg/day have been well tolerated in open studies of OCD. The maximum fluoxetine dose should not exceed 80 mg/day.

Pediatric (children and adolescents) — In the controlled clinical trial of fluoxetine supporting its effectiveness in the treatment of OCD, patients were administered fluoxetine doses in the range of 10 to 60 mg/day (see CLINICAL TRIALS).

In adolescents and higher weight children, treatment should be initiated with a dose of 10 mg/day. After 2 weeks, the dose should be increased to 20 mg/day. Additional dose increases may be considered after several more weeks if insufficient clinical improvement is observed. A dose range of 20 to 60 mg/day is recommended.

In lower weight children, treatment should be initiated with a dose of 10 mg/day. Additional dose increases may be considered after several more weeks if insufficient clinical improvement is observed. A dose range of 20 to 30 mg/day is recommended. Experience with daily doses greater than 20 mg is very minimal, and there is no experience with doses greater than 60 mg.

All patients — As with the use of Prozac in the treatment of major depressive disorder, a lower or less frequent dosage should be used in patients with hepatic impairment. A lower or less frequent dosage should also be considered for the elderly (see Geriatric Use under PRECAUTIONS), and for patients with concurrent disease or on multiple concomitant medications. Dosage adjustments for renal impairment are not routinely necessary (see Liver disease and Renal disease under CLINICAL PHARMACOLOGY, and Use in Patients with Concomitant Illness under PRECAUTIONS).

Maintenance/Continuation Treatment

While there are no systematic studies that answer the question of how long to continue Prozac, OCD is a chronic condition and it is reasonable to consider continuation for a responding patient. Although the efficacy of Prozac after 13 weeks has not been documented in controlled trials, adult patients have been continued in therapy under double–blind conditions for up to an additional 6 months without loss of benefit. However, dosage adjustments should be made to maintain the patient on the lowest effective dosage, and patients should be periodically reassessed to determine the need for treatment.

Bulimia Nervosa Initial Treatment

In the controlled clinical trials of fluoxetine supporting its effectiveness in the treatment of bulimia nervosa, patients were administered fixed daily fluoxetine doses of 20 or 60 mg, or placebo (see CLINICAL TRIALS). Only the 60–mg dose was statistically significantly superior to placebo in reducing the frequency of binge–eating and vomiting. Consequently, the recommended dose is 60 mg/day, administered in the morning. For some patients it may be advisable to titrate up to this target dose over several days. Fluoxetine doses above 60 mg/day have not been systematically studied in patients with bulimia.

As with the use of Prozac in the treatment of major depressive disorder and OCD, a lower or less frequent dosage should be used in patients with hepatic impairment. A lower or less frequent dosage should also be considered for the elderly (see Geriatric Use under PRECAUTIONS), and for patients with concurrent disease or on multiple concomitant medications. Dosage adjustments for renal impairment are not routinely necessary (see Liver disease and Renal disease under CLINICAL PHARMACOLOGY, and Use in Patients with Concomitant Illness under PRECAUTIONS).

Maintenance/Continuation Treatment

Systematic evaluation of continuing Prozac 60 mg/day for periods of up to 52 weeks in patients with bulimia who have responded while taking Prozac 60 mg/day during an 8–week acute treatment phase has demonstrated a benefit of such maintenance treatment (see CLINICAL TRIALS). Nevertheless, patients should be periodically reassessed to determine the need for maintenance treatment.

Panic Disorder Initial Treatment

In the controlled clinical trials of fluoxetine supporting its effectiveness in the treatment of panic disorder, patients were administered fluoxetine doses in the range of 10 to 60 mg/day (see CLINICAL TRIALS). Treatment should be initiated with a dose of 10 mg/day. After 1 week, the dose should be increased to 20 mg/day. The most frequently administered dose in the 2 flexible–dose clinical trials was 20 mg/day.

A dose increase may be considered after several weeks if no clinical improvement is observed. Fluoxetine doses above 60 mg/day have not been systematically evaluated in patients with panic disorder.

As with the use of Prozac in other indications, a lower or less frequent dosage should be used in patients with hepatic impairment. A lower or less frequent dosage should also be considered for the elderly (see Geriatric Use under PRECAUTIONS), and for patients with concurrent disease or on multiple concomitant medications. Dosage adjustments for renal impairment are not routinely necessary (see Liver disease and Renal disease under CLINICAL PHARMACOLOGY, and Use in Patients with Concomitant Illness under PRECAUTIONS).

Maintenance/Continuation Treatment

While there are no systematic studies that answer the question of how long to continue Prozac, panic disorder is a chronic condition and it is reasonable to consider continuation for a responding patient. Nevertheless, patients should be periodically reassessed to determine the need for continued treatment.

Special Populations Treatment of Pregnant Women During the Third Trimester

Neonates exposed to Prozac and other SSRIs or SNRIs, late in the third trimester have developed complications requiring prolonged hospitalization, respiratory support, and tube feeding (see PRECAUTIONS). When treating pregnant women with Prozac during the third trimester, the physician should carefully consider the potential risks and benefits of treatment. The physician may consider tapering Prozac in the third trimester.

Discontinuation of Treatment with Prozac

Symptoms associated with discontinuation of Prozac and other SSRIs and SNRIs, have been reported (see PRECAUTIONS). Patients should be monitored for these symptoms when discontinuing treatment. A gradual reduction in the dose rather than abrupt cessation is recommended whenever possible. If intolerable symptoms occur following a decrease in the dose or upon discontinuation of treatment, then resuming the previously prescribed dose may be considered. Subsequently, the physician may continue decreasing the dose but at a more gradual rate. Plasma fluoxetine and norfluoxetine concentration decrease gradually at the conclusion of therapy which may minimize the risk of discontinuation symptoms with this drug.

Information for Patients

Prescribers or other health professionals should inform patients, their families, and their caregivers about the benefits and risks associated with treatment with Prozac and should counsel them in its appropriate use. A patient Medication Guide about“Antidepressant Medicines, Depression and other Serious Mental Illnesses, and Suicidal Thoughts or Actions” is available for Prozac. The prescriber or health professional should instruct patients, their families, and their caregivers to read the Medication Guide and should assist them in understanding its contents. Patients should be given the opportunity to discuss the contents of the Medication Guide and to obtain answers to any questions they may have. The complete text of the Medication Guide is reprinted at the end of this document.

Patients should be advised of the following issues and asked to alert their prescriber if these occur while taking Prozac.

Clinical Worsening and Suicide Risk — Patients, their families, and their caregivers should be encouraged to be alert to the emergence of anxiety, agitation, panic attacks, insomnia, irritability, hostility, aggressiveness, impulsivity, akathisia (psychomotor restlessness), hypomania, mania, other unusual changes in behavior, worsening of depression, and suicidal ideation, especially early during antidepressant treatment and when the dose is adjusted up or down. Families and caregivers of patients should be advised to look for the emergence of such symptoms on a day–to–day basis, since changes may be abrupt. Such symptoms should be reported to the patient’s prescriber or health professional, especially if they are severe, abrupt in onset, or were not part of the patient’s presenting symptoms. Symptoms such as these may be associated with an increased risk for suicidal thinking and behavior and indicate a need for very close monitoring and possibly changes in the medication.

Serotonin Syndrome — Patients should be cautioned about the risk of serotonin syndrome with the concomitant use of Prozac and triptans, tramadol or other serotonergic agents.

Because Prozac may impair judgment, thinking, or motor skills, patients should be advised to avoid driving a car or operating hazardous machinery until they are reasonably certain that their performance is not affected.

Patients should be advised to inform their physician if they are taking or plan to take any prescription or over–the–counter drugs, or alcohol.

Abnormal Bleeding- Patients should be cautioned about the concomitant use of fluoxetine and NSAIDs, aspirin, warfarin, or other drugs that affect coagulation since combined use of psychotropic drugs that interfere with serotonin reuptake and these agents have been associated with an increased risk of bleeding (see PRECAUTIONS, Abnormal Bleeding).

Patients should be advised to notify their physician if they become pregnant or intend to become pregnant during therapy.

Patients should be advised to notify their physician if they are breast–feeding an infant.

Patients should be advised to notify their physician if they develop a rash or hives.

Laboratory Tests

There are no specific laboratory tests recommended.

Drug Interactions

As with all drugs, the potential for interaction by a variety of mechanisms (e.g., pharmacodynamic, pharmacokinetic drug inhibition or enhancement, etc.) is a possibility (see Accumulation and slow elimination under CLINICAL PHARMACOLOGY).

Drugs metabolized by CYP2D6 — Fluoxetine inhibits the activity of CYP2D6, and may make individuals with normal CYP2D6 metabolic activity resemble a poor metabolizer. Coadministration of fluoxetine with other drugs that are metabolized by CYP2D6, including certain antidepressants (e.g., TCAs), antipsychotics (e.g., phenothiazines and most atypicals), and antiarrhythmics (e.g., propafenone, flecainide, and others) should be approached with caution. Therapy with medications that are predominantly metabolized by the CYP2D6 system and that have a relatively narrow therapeutic index (see list below) should be initiated at the low end of the dose range if a patient is receiving fluoxetine concurrently or has taken it in the previous 5 weeks. Thus, his/her dosing requirements resemble those of poor metabolizers. If fluoxetine is added to the treatment regimen of a patient already receiving a drug metabolized by CYP2D6, the need for decreased dose of the original medication should be considered. Drugs with a narrow therapeutic index represent the greatest concern (e.g., flecainide, propafenone, vinblastine, and TCAs). Due to the risk of serious ventricular arrhythmias and sudden death potentially associated with elevated plasma levels of thioridazine, thioridazine should not be administered with fluoxetine or within a minimum of 5 weeks after fluoxetine has been discontinued (see CONTRAINDICATIONS and WARNINGS).

Drugs metabolized by CYP3A4 — In an in vivo interaction study involving coadministration of fluoxetine with single doses of terfenadine (a CYP3A4 substrate), no increase in plasma terfenadine concentrations occurred with concomitant fluoxetine. In addition, in vitro studies have shown ketoconazole, a potent inhibitor of CYP3A4 activity, to be at least 100 times more potent than fluoxetine or norfluoxetine as an inhibitor of the metabolism of several substrates for this enzyme, including astemizole, cisapride, and midazolam. These data indicate that fluoxetine’s extent of inhibition of CYP3A4 activity is not likely to be of clinical significance.

CNS active drugs — The risk of using Prozac in combination with other CNS active drugs has not been systematically evaluated. Nonetheless, caution is advised if the concomitant administration of Prozac and such drugs is required. In evaluating individual cases, consideration should be given to using lower initial doses of the concomitantly administered drugs, using conservative titration schedules, and monitoring of clinical status (see Accumulation and slow elimination under CLINICAL PHARMACOLOGY).

Anticonvulsants — Patients on stable doses of phenytoin and carbamazepine have developed elevated plasma anticonvulsant concentrations and clinical anticonvulsant toxicity following initiation of concomitant fluoxetine treatment.

Antipsychotics — Some clinical data suggests a possible pharmacodynamic and/or pharmacokinetic interaction between SSRIs and antipsychotics. Elevation of blood levels of haloperidol and clozapine has been observed in patients receiving concomitant fluoxetine. Clinical studies of pimozide with other antidepressants demonstrate an increase in drug interaction or QTc prolongation. While a specific study with pimozide and fluoxetine has not been conducted, the potential for drug interactions or QTc prolongation warrants restricting the concurrent use of pimozide and Prozac. Concomitant use of Prozac and pimozide is contraindicated (see CONTRAINDICATIONS). For thioridazine, see CONTRAINDICATIONS and WARNINGS.

Benzodiazepines — The half–life of concurrently administered diazepam may be prolonged in some patients (see Accumulation and slow elimination under CLINICAL PHARMACOLOGY). Coadministration of alprazolam and fluoxetine has resulted in increased alprazolam plasma concentrations and in further psychomotor performance decrement due to increased alprazolam levels.

Lithium — There have been reports of both increased and decreased lithium levels when lithium was used concomitantly with fluoxetine. Cases of lithium toxicity and increased serotonergic effects have been reported. Lithium levels should be monitored when these drugs are administered concomitantly.

Tryptophan — Five patients receiving Prozac in combination with tryptophan experienced adverse reactions, including agitation, restlessness, and gastrointestinal distress.

Monoamine oxidase inhibitors — See CONTRAINDICATIONS.

Other drugs effective in the treatment of major depressive disorder — In 2 studies, previously stable plasma levels of imipramine and desipramine have increased greater than 2– to 10–fold when fluoxetine has been administered in combination. This influence may persist for 3 weeks or longer after fluoxetine is discontinued. Thus, the dose of TCA may need to be reduced and plasma TCA concentrations may need to be monitored temporarily when fluoxetine is coadministered or has been recently discontinued (see Accumulation and slow elimination under CLINICAL PHARMACOLOGY, and Drugs metabolized by CYP2D6 under Drug Interactions).

Serotonergic drugs — Based on the mechanism of action of SNRIs and SSRIs, including Prozac, and the potential for serotonin syndrome, caution is advised when Prozac is coadministered with other drugs that may affect the serotonergic neurotransmitter systems, such as triptans, linezolid (an antibiotic which is a reversible non–selective MAOI), lithium, tramadol, or St. John’s Wort (see Serotonin Syndrome under WARNINGS). The concomitant use of Prozac with other SSRIs, SNRIs or tryptophan is not recommended (see Tryptophan).

Triptans — There have been rare postmarketing reports of serotonin syndrome with use of an SSRI and a triptan. If concomitant treatment of Prozac with a triptan is clinically warranted, careful observation of the patient is advised, particularly during treatment initiation and dose increases (see Serotonin Syndrome under WARNINGS).

Potential effects of coadministration of drugs tightly bound to plasma proteins — Because fluoxetine is tightly bound to plasma protein, the administration of fluoxetine to a patient taking another drug that is tightly bound to protein (e.g., Coumadin, digitoxin) may cause a shift in plasma concentrations potentially resulting in an adverse effect. Conversely, adverse effects may result from displacement of protein–bound fluoxetine by other tightly–bound drugs (see Accumulation and slow elimination under CLINICAL PHARMACOLOGY).

Drugs that interfere with hemostasis (e.g., NSAIDs, Aspirin, Warfarin) — Serotonin release by platelets plays an important role in hemostasis. Epidemiological studies of the case–control and cohort design that have demonstrated an association between use of psychotropic drugs that interfere with serotonin reuptake and the occurrence of upper gastrointestinal bleeding have also shown that concurrent use of an NSAID or aspirin may potentiate this risk of bleeding. Altered anticoagulant effects, including increased bleeding, have been reported when SSRIs or SNRIs are coadministered with warfarin. Patients receiving warfarin therapy should be carefully monitored when fluoxetine is initiated or discontinued.

Electroconvulsive therapy (ECT) — There are no clinical studies establishing the benefit of the combined use of ECT and fluoxetine. There have been rare reports of prolonged seizures in patients on fluoxetine receiving ECT treatment.

Carcinogenesis, Mutagenesis, Impairment of Fertility

There is no evidence of carcinogenicity or mutagenicity from in vitro or animal studies. Impairment of fertility in adult animals at doses up to 12.5 mg/kg/day (approximately 1.5 times the MRHD on a mg/m^2 basis) was not observed.

Carcinogenicity — The dietary administration of fluoxetine to rats and mice for 2 years at doses of up to 10 and 12 mg/kg/day, respectively [approximately 1.2 and 0.7 times, respectively, the maximum recommended human dose (MRHD) of 80 mg on a mg/m^2 basis], produced no evidence of carcinogenicity.

Mutagenicity — Fluoxetine and norfluoxetine have been shown to have no genotoxic effects based on the following assays: bacterial mutation assay, DNA repair assay in cultured rat hepatocytes, mouse lymphoma assay, and in vivo sister chromatid exchange assay in Chinese hamster bone marrow cells.

Impairment of fertility — Two fertility studies conducted in adult rats at doses of up to 7.5 and 12.5 mg/kg/day (approximately 0.9 and 1.5 times the MRHD on a mg/m^2 basis) indicated that fluoxetine had no adverse effects on fertility (see Pediatric Use).

Pregnancy Pregnancy Category C

In embryo–fetal development studies in rats and rabbits, there was no evidence of teratogenicity following administration of up to 12.5 and 15 mg/kg/day, respectively (1.5 and 3.6 times, respectively, the MRHD of 80 mg on a mg/m^2 basis) throughout organogenesis. However, in rat reproduction studies, an increase in stillborn pups, a decrease in pup weight, and an increase in pup deaths during the first 7 days postpartum occurred following maternal exposure to 12 mg/kg/day (1.5 times the MRHD on a mg/m^2 basis) during gestation or 7.5 mg/kg/day (0.9 times the MRHD on a mg/m^2 basis) during gestation and lactation. There was no evidence of developmental neurotoxicity in the surviving offspring of rats treated with 12 mg/kg/day during gestation. The no–effect dose for rat pup mortality was 5 mg/kg/day (0.6 times the MRHD on a mg/m^2 basis). Prozac should be used during pregnancy only if the potential benefit justifies the potential risk to the fetus.

Nonteratogenic Effects

Neonates exposed to Prozac and other SSRIs or serotonin and norepinephrine reuptake inhibitors (SNRIs), late in the third trimester have developed complications requiring prolonged hospitalization, respiratory support, and tube feeding. Such complications can arise immediately upon delivery. Reported clinical findings have included respiratory distress, cyanosis, apnea, seizures, temperature instability, feeding difficulty, vomiting, hypoglycemia, hypotonia, hypertonia, hyperreflexia, tremor, jitteriness, irritability, and constant crying. These features are consistent with either a direct toxic effect of SSRIs and SNRIs or, possibly, a drug discontinuation syndrome. It should be noted that, in some cases, the clinical picture is consistent with serotonin syndrome (see Monoamine oxidase inhibitors under CONTRAINDICATIONS).

Infants exposed to SSRIs in late pregnancy may have an increased risk for persistent pulmonary hypertension of the newborn (PPHN). PPHN occurs in 1–2 per 1000 live births in the general population and is associated with substantial neonatal morbidity and mortality. In a retrospective case–control study of 377 women whose infants were born with PPHN and 836 women whose infants were born healthy, the risk for developing PPHN was approximately six–fold higher for infants exposed to SSRIs after the 20th week of gestation compared to infants who had not been exposed to antidepressants during pregnancy. There is currently no corroborative evidence regarding the risk for PPHN following exposure to SSRIs in pregnancy; this is the first study that has investigated the potential risk. The study did not include enough cases with exposure to individual SSRIs to determine if all SSRIs posed similar levels of PPHN risk.

When treating a pregnant woman with Prozac during the third trimester, the physician should carefully consider both the potential risks and benefits of treatment (see DOSAGE AND ADMINISTRATION). Physicians should note that in a prospective longitudinal study of 201 women with a history of major depression who were euthymic at the beginning of pregnancy, women who discontinued antidepressant medication during pregnancy were more likely to experience a relapse of major depression than women who continued antidepressant medication.

Labor and Delivery

The effect of Prozac on labor and delivery in humans is unknown. However, because fluoxetine crosses the placenta and because of the possibility that fluoxetine may have adverse effects on the newborn, fluoxetine should be used during labor and delivery only if the potential benefit justifies the potential risk to the fetus.

Nursing Mothers

Because Prozac is excreted in human milk, nursing while on Prozac is not recommended. In one breast–milk sample, the concentration of fluoxetine plus norfluoxetine was 70.4 ng/mL. The concentration in the mother’s plasma was 295.0 ng/mL. No adverse effects on the infant were reported. In another case, an infant nursed by a mother on Prozac developed crying, sleep disturbance, vomiting, and watery stools. The infant’s plasma drug levels were 340 ng/mL of fluoxetine and 208 ng/mL of norfluoxetine on the second day of feeding.

Pediatric Use

The efficacy of Prozac for the treatment of major depressive disorder was demonstrated in two 8– to 9–week placebo–controlled clinical trials with 315 pediatric outpatients ages 8 to ≤18 (see CLINICAL TRIALS).

Medication Guide
Antidepressant Medicines, Depression and other Serious Mental Illnesses, and Suicidal Thoughts or Actions

Read the Medication Guide that comes with your or your family member’s antidepressant medicine. This Medication Guide is only about the risk of suicidal thoughts and actions with antidepressant medicines. Talk to your, or your family member’s, healthcare provider about:

- all risks and benefits of treatment with antidepressant medicines
- all treatment choices for depression or other serious mental illness

What is the most important information I should know about antidepressant medicines, depression and other serious mental illnesses, and suicidal thoughts or actions?

1. Antidepressant medicines may increase suicidal thoughts or actions in some children, teenagers, and young adults within the first few months of treatment.
2. Depression and other serious mental illnesses are the most important causes of suicidal thoughts and actions. Some people may have a particularly high risk of having suicidal thoughts or actions. These include people who have (or have a family history of) bipolar illness (also called manic–depressive illness) or suicidal thoughts or actions.
3. How can I watch for and try to prevent suicidal thoughts and actions in myself or a family member?
  - Pay close attention to any changes, especially sudden changes, in mood, behaviors, thoughts, or feelings. This is very important when an antidepressant medicine is started or when the dose is changed.
  - Call the healthcare provider right away to report new or sudden changes in mood, behavior, thoughts, or feelings.
  - Keep all follow-up visits with the healthcare provider as scheduled. Call the healthcare provider between visits as needed, especially if you have concerns about symptoms.

Call a healthcare provider right away if you or your family member has any of the following symptoms, especially if they are new, worse, or worry you:

- thoughts about suicide or dying
- attempts to commit suicide
- new or worse depression
- new or worse anxiety
- feeling very agitated or restless
- panic attacks
- trouble sleeping (insomnia)
- new or worse irritability
- acting aggressive, being angry, or violent
- acting on dangerous impulses
- an extreme increase in activity and talking (mania)
- other unusual changes in behavior or mood

What else do I need to know about antidepressant medicines?

- Never stop an antidepressant medicine without first talking to a healthcare provider. Stopping an antidepressant medicine suddenly can cause other symptoms.
- Antidepressants are medicines used to treat depression and other illnesses. It is important to discuss all the risks of treating depression and also the risks of not treating it. Patients and their families or other caregivers should discuss all treatment choices with the healthcare provider, not just the use of antidepressants.
- Antidepressant medicines have other side effects. Talk to the healthcare provider about the side effects of the medicine prescribed for you or your family member.
- Antidepressant medicines can interact with other medicines. Know all of the medicines that you or your family member takes. Keep a list of all medicines to show the healthcare provider. Do not start new medicines without first checking with your healthcare provider.
- Not all antidepressant medicines prescribed for children are FDA approved for use in children. Talk to your child’s healthcare provider for more information.

This Medication Guide has been approved by the US Food and Drug Administration for all antidepressants.

Patient Information revised June 21, 2007

PV 5083 AMP

WARNING

Suicidality and Antidepressant Drugs — Antidepressants increased the risk compared to placebo of suicidal thinking and behavior (suicidality) in children, adolescents, and young adults in short–term studies of major depressive disorder (MDD) and other psychiatric disorders. Anyone considering the use of Prozac or any other antidepressant in a child, adolescent, or young adult must balance this risk with the clinical need. Short–term studies did not show an increase in the risk of suicidality with antidepressants compared to placebo in adults beyond age 24; there was a reduction in risk with antidepressants compared to placebo in adults aged 65 and older. Depression and certain other psychiatric disorders are themselves associated with increases in the risk of suicide. Patients of all ages who are started on antidepressant therapy should be monitored appropriately and observed closely for clinical worsening, suicidality, or unusual changes in behavior. Families and caregivers should be advised of the need for close observation and communication with the prescriber. Prozac is approved for use in pediatric patients with MDD and obsessive compulsive disorder (OCD). (See WARNINGS, Clinical Worsening and Suicide Risk, PRECAUTIONS, Information for Patients, and PRECAUTIONS, Pediatric Use.)

DESCRIPTION

Prozac® (fluoxetine capsules, USP and fluoxetine oral solution, USP) is a psychotropic drug for oral administration. It is also marketed for the treatment of premenstrual dysphoric disorder (Sarafem®, fluoxetine hydrochloride). It is designated (±)-N-methyl-3-phenyl-3-[(α,α,α-trifluoro-p-tolyl)oxy]propylamine hydrochloride and has the empirical formula of C17H18F3NO•HCl. Its molecular weight is 345.79. The structural formula is:

Fluoxetine hydrochloride is a white to off–white crystalline solid with a solubility of 14 mg/mL in water.

Each Pulvule® contains fluoxetine hydrochloride equivalent to 10 mg (32.3 μmol), 20 mg (64.7 μmol), or 40 mg (129.3 μmol) of fluoxetine. The Pulvules also contain starch, gelatin, silicone, titanium dioxide, iron oxide, and other inactive ingredients. The 10– and 20–mg Pulvules also contain FDandC Blue No. 1, and the 40–mg Pulvule also contains FDnadC Blue No. 1 and FDandC Yellow No. 6.

The oral solution contains fluoxetine hydrochloride equivalent to 20 mg/5 mL (64.7 μmol) of fluoxetine. It also contains alcohol 0.23%, benzoic acid, flavoring agent, glycerin, purified water, and sucrose.

Prozac Weekly™ capsules, a delayed–release formulation, contain enteric–coated pellets of fluoxetine hydrochloride equivalent to 90 mg (291 μmol) of fluoxetine. The capsules also contain DandC Yellow No. 10, FDandC Blue No. 2, gelatin, hypromellose, hypromellose acetate succinate, sodium lauryl sulfate, sucrose, sugar spheres, talc, titanium dioxide, triethyl citrate, and other inactive ingredients.

PROZAC 20MG Package Label